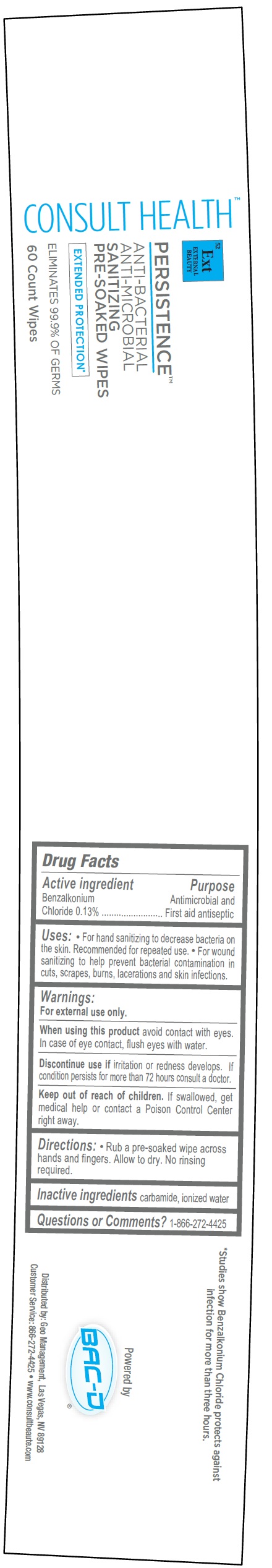 DRUG LABEL: Consult Health Persistence Hand Sanitizer
NDC: 70803-005 | Form: CLOTH
Manufacturer: Geo Management Corporation
Category: otc | Type: HUMAN OTC DRUG LABEL
Date: 20210723

ACTIVE INGREDIENTS: BENZALKONIUM CHLORIDE 1.3 mg/1 g
INACTIVE INGREDIENTS: UREA; WATER

Consult Health Persistence Hand Sanitizer Wipes

Active ingredient

Benzalkonium Chloride 0.13%

Purpose

Antimicrobial and First aid antiseptic

Uses:

• For hand sanitizing to decrease bacteria on the skin. Recommended for repeated use. • For wound sanitizing to help prevent bacterial contamination in cuts, scrapes, burns, lacerations and skin infections.

Warnings:

For external use only.

When using this product

avoid contact with eyes. In case of eye contact, flush eyes with water.

Discontinue use if

irritation or redness develops. If condition persists for more than 72 hours consult a doctor.

Keep out of reach of children.

If swallowed, get medical help or contact a Poison Control Center right away.

Directions:

• Rub a pre-soaked wipe across hands and fingers. Allow to dry. No rinsing required.

Inactive ingredients

carbamide, ionized water

Questions or Comments?

1-866-272-4425